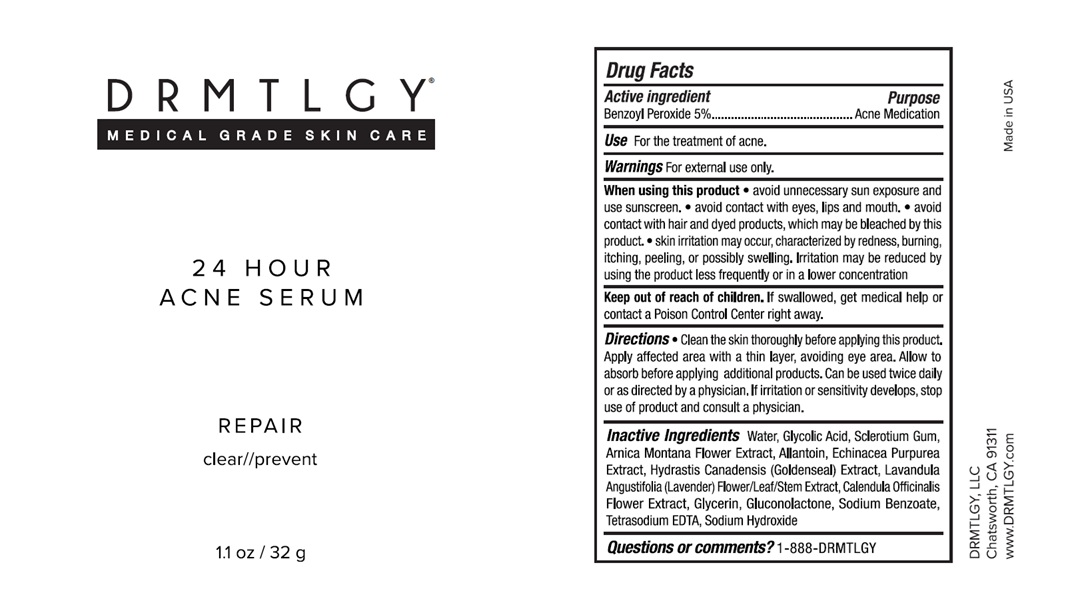 DRUG LABEL: 24 Hour Acne Serum 
NDC: 83286-007 | Form: GEL
Manufacturer: Drmtlgy, LLC
Category: otc | Type: HUMAN OTC DRUG LABEL
Date: 20250408

ACTIVE INGREDIENTS: BENZOYL PEROXIDE 5 g/100 g
INACTIVE INGREDIENTS: WATER; GLYCOLIC ACID; BETASIZOFIRAN; ARNICA MONTANA FLOWER; ALLANTOIN; ECHINACEA PURPUREA WHOLE; GOLDENSEAL; LAVANDULA ANGUSTIFOLIA SUBSP. ANGUSTIFOLIA FLOWERING TOP; CALENDULA OFFICINALIS FLOWER; GLYCERIN; GLUCONOLACTONE; SODIUM BENZOATE; EDETATE SODIUM; SODIUM HYDROXIDE

DRMTLGY® 24 Hour Acne Serum

Active ingredient

Benzoyl Peroxide 5%

Purpose

Acne Medication

Use

For the treatment of acne.

Warnings

For external use only.

When using this product • avoid unnecessary sun exposure and use sunscreen. • avoid contact with eyes, lips and mouth. • avoid contact with hair and dyed products, which may be bleached by this product. • skin irritation may occur, characterized by redness, burning, itching, peeling, or possibly swelling. Irritation may be reduced by using the product less frequently or in a lower concentration

Keep out of reach of children. If swallowed, get medical help or contact a Poison Control Center right away.

Directions

• Clean the skin thoroughly before applying this product. Apply affected area with a thin layer, avoiding eye area. Allow to absorb before applying additional products. Can be used twice daily or as directed by a physician. If irritation or sensitivity develops, stop use of product and consult a physician.

Inactive Ingredients

Water, Glycolic Acid, Sclerotium Gum, Arnica Montana Flower Extract, Allantoin, Echinacea Purpurea Extract, Hydrastis Canadensis (Goldenseal) Extract, Lavandula Angustifolia (Lavender) Flower/Leaf/Stem Extract, Calendula Officinalis Flower Extract, Glycerin, Gluconolactone, Sodium Benzoate, Tetrasodium EDTA, Sodium Hydroxide

Questions or comments?

1-888-DRMTLGY

MEDICAL GRADE SKIN CARE

REPAIR

clear//prevent

DRMTLGY, LLC
Chatsworth, CA 91311
www.DRMTLGY.com

Made in USA